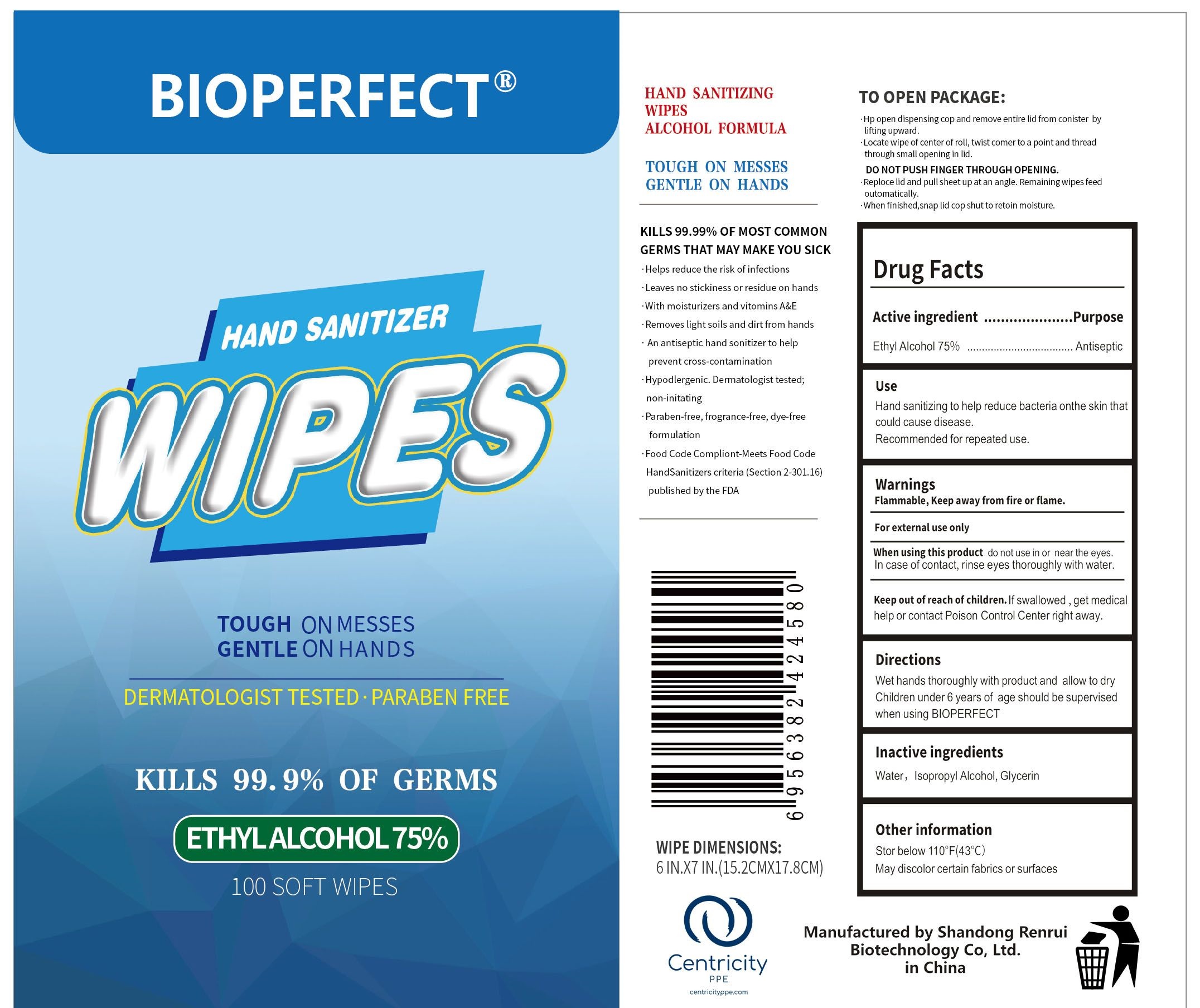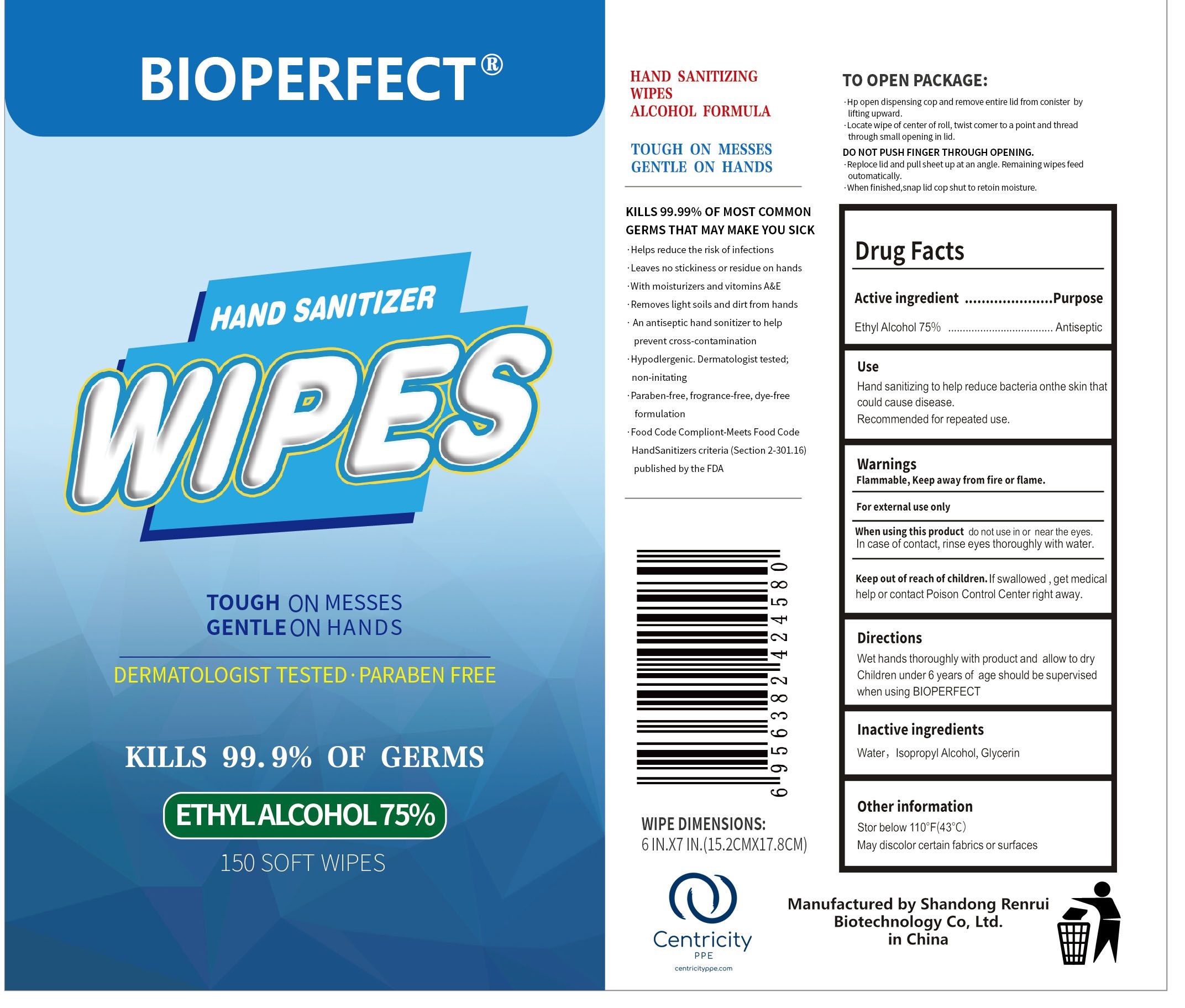 DRUG LABEL: BIOPERFECT Hand Sanitizer Wipes (75% Alcohol)
NDC: 77985-002 | Form: CLOTH
Manufacturer: Shandong Renrui Biotechnology Co, Ltd.
Category: otc | Type: HUMAN OTC DRUG LABEL
Date: 20200828

ACTIVE INGREDIENTS: ALCOHOL 0.75 mL/1 mL
INACTIVE INGREDIENTS: WATER; ISOPROPYL ALCOHOL; GLYCERIN

BIOPERFECT Hand Sanitizer Wipes (75% Alcohol)

Active ingredient

Ethyl Alcohol 75%

Purpose

Antiseptic

Use

Hand sanitizing to help reduce bacteria onthe skin that could cause disease.Recommended for repeated use.

Warnings

Flammable, Keep away from fire or flame.

For external use only

When using this product

do not use in or near the eyes. In case of contact, rinse eyes thoroughly with water.

Keep out of reach of children.

If swallowed, get medical help or contact Poison Control Center right away.

Directions

Wet hands thoroughly with product and allow to dry. Children under 6 years of age should be supervised when using BIOPERFECT

Inactive ingredients

Water, Isopropyl Alcohol, Glycerin

Other information

Store below 110°F(43°C)

May discolor certain fabrics or surfaces